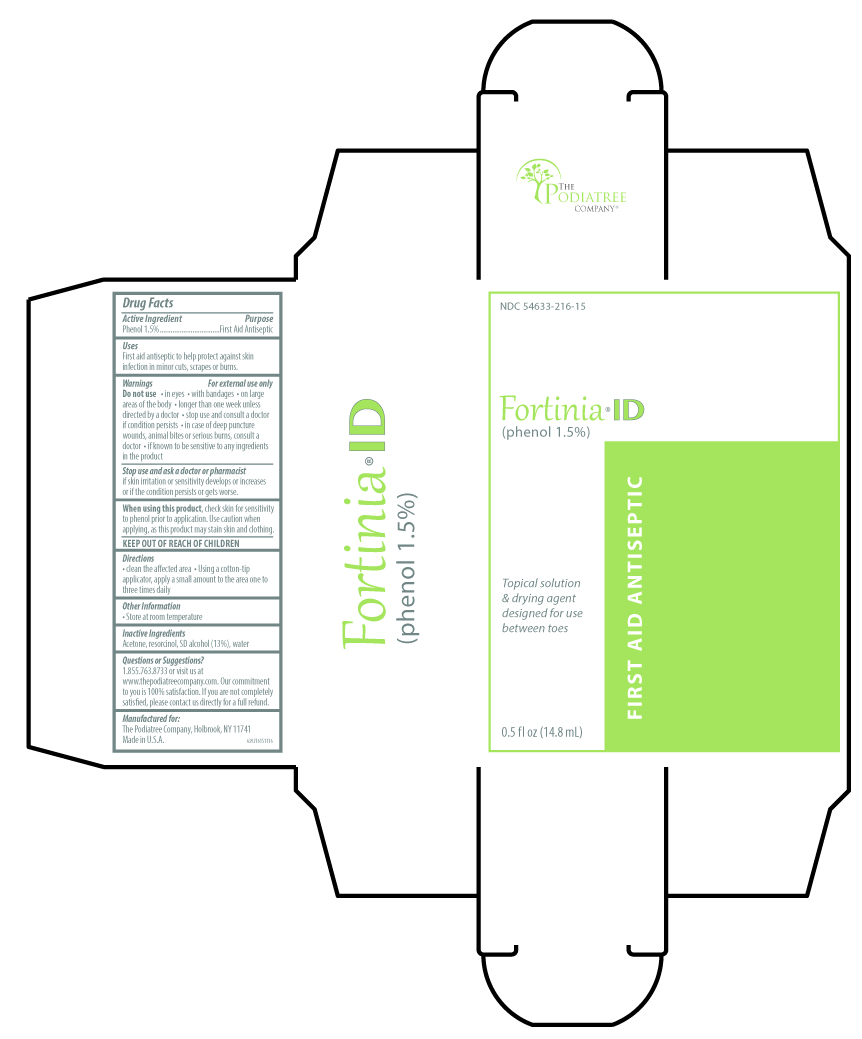 DRUG LABEL: Fortinia ID
NDC: 54633-216 | Form: LIQUID
Manufacturer: The Podiatree Company
Category: otc | Type: HUMAN OTC DRUG LABEL
Date: 20260108

ACTIVE INGREDIENTS: PHENOL 1.5 g/100 mL
INACTIVE INGREDIENTS: ACETONE; RESORCINOL; ALCOHOL; WATER

Drug Facts

Active Ingredient

Phenol 1.5%

Purpose

First Aid Antiseptic

Uses

- First aid antiseptic to help protect against skin infection in minor cuts, scrapes or burns

Warnings

For external use only

Do not use

- in eyes
- with bandages
- on large areas of the body
- longer than one week unless directed by a doctor
- stop use and consult a doctor if condition persists
- in case of deep puncture wounds, animal bites, or serious burns, consult a doctor
- if known to be sensitive to any ingredients in this product

Stop use and ask a doctor or pharmacist if skin irritation or sensitivity develops or increases or if the condition persists or gets worse.

When using this product

- Check skin for sensitivity to phenol prior to application
- Use caution when applying as this product will stain skin and clothing

KEEP OUT OF REACH OF CHILDREN

Directions

- clean the affected area
- apply a small amount on the area one to three times daily

Other Information

Store at controlled room temperature

Inactive Ingredients

Acetone, resorcinol, SD alcohol (13%), water

Questions or Suggestions?

1.855.763.8733 or visit us at www.thepodiatreecompany.com. Our commitment to you is 100% satisfaction. If you are not

completely satisfied, please contact us directly for a full refund.